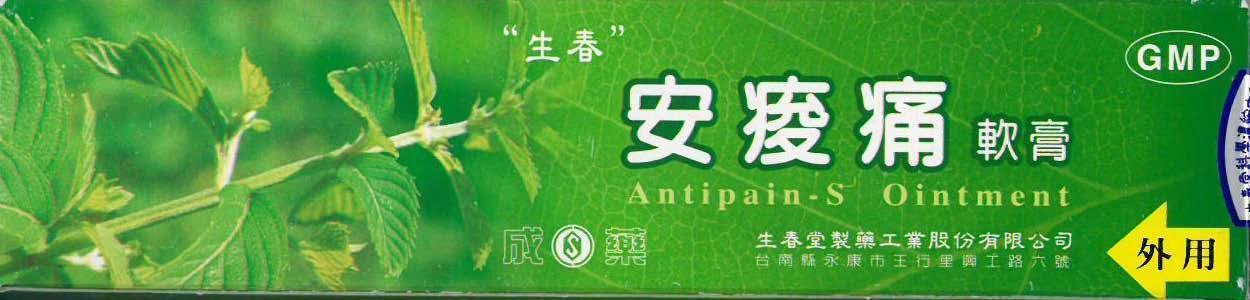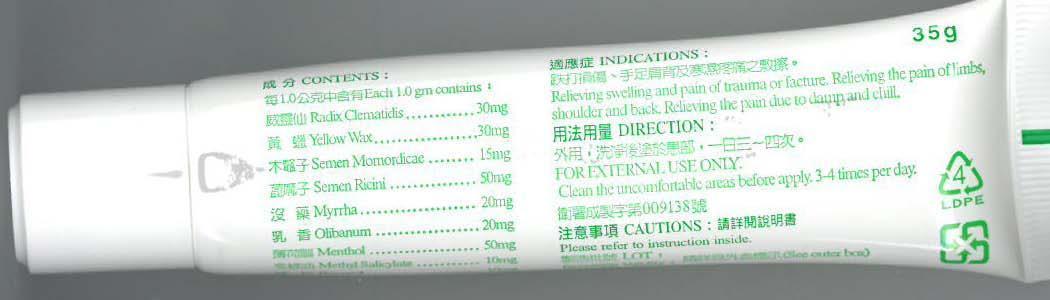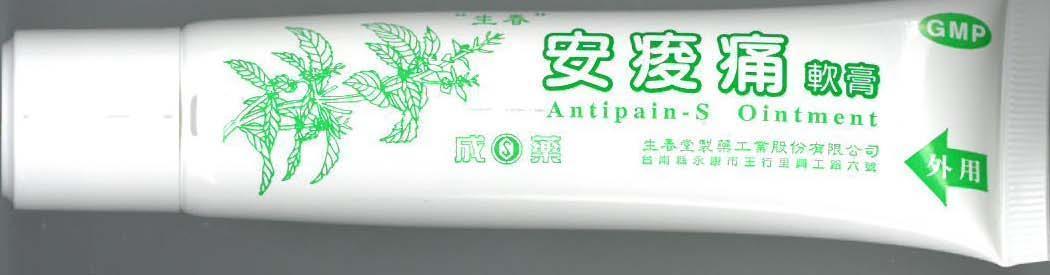 DRUG LABEL: ANTIPAIN-S
NDC: 69165-201 | Form: OINTMENT
Manufacturer: GEORGE L. RODRIGUEZ M.D., PC
Category: homeopathic | Type: HUMAN OTC DRUG LABEL
Date: 20140812

ACTIVE INGREDIENTS: CLEMATIS HEXAPETALA WHOLE 30 mg/1 g; MOMORDICA CHARANTIA WHOLE 15 mg/1 g; MYRRH 20 mg/1 g; FRANKINCENSE OIL 20 mg/1 g; MENTHOL 50 mg/1 g
INACTIVE INGREDIENTS: YELLOW WAX; RICINUS COMMUNIS WHOLE; PETROLATUM

ACTIVE INGREDIENT

CONTENTS:

EACH 1.0 GM CONTAINS:

RADIX CLEMENTIS.....30 MG

YELLOW WAX.....30 MG

SEMEN MOMORDICAE.....15 MG

SEMEN RICINI.....50 MG

MYRRHA.....20 MG

OLIBANUM.....20 MG

MENTHOL.....50 MG

METHYL SALICYLATE.....10 MG

PURPOSE

PAIN RELIEF

WARNINGS

CAUTIONS:

DO NOT USE THIS PRODUCT IF YOU HAVE A SENSITIVE SKIN.

DO NOT APPLY TO THE WOUNDED OR DAMAGED SKIN.

AVOID EYE CONTACT.

DISCONTINUE USE IF SIGNS OF IRRITATION APPEAR. IF IRRITATION PERSISTS, CONSULT A DOCTOR. IF YOU ARE ALLERGIC TO ANY INGREDIENT IN THE PRODUCT, DO NOT USE.

INDICATIONS AND USAGE

RELIEVING SWELLING AND PAIN OF TRAUMA OR FRACTURE. RELIEVING THE PAIN OF LIMBS, SHOULDER AND BACK. RELIEVNG THE PAIN DUE TO DAMP AND CHILL.

DIRECTIONS:

FOR EXTERNAL USE ONLY.

CLEAN THE UNCOMFORTABLE AREAS BEFORE APPLY. 3-4 TIMES PER DAY.

KEEP OUT OF REACH OF CHILDREN.

INACTIVE INGREDIENT

YELLOW WAX.....30 MG

SEMEN RICINI.....50 MG

PETROLATUM